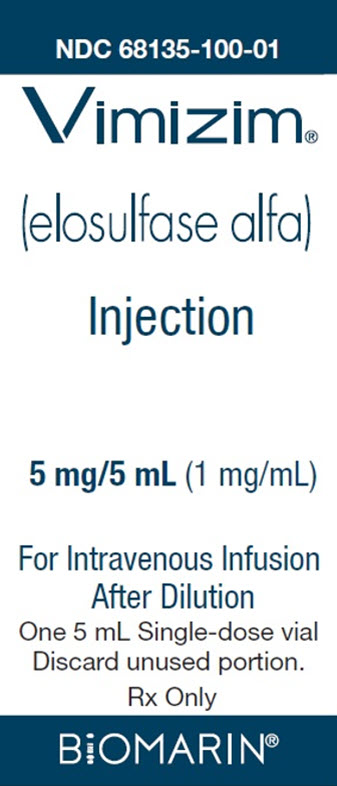 DRUG LABEL: VIMIZIM
NDC: 68135-100 | Form: INJECTION, SOLUTION, CONCENTRATE
Manufacturer: BioMarin Pharmaceutical Inc.
Category: prescription | Type: HUMAN PRESCRIPTION DRUG LABEL
Date: 20251030

ACTIVE INGREDIENTS: ELOSULFASE ALFA 5 mg/5 mL

HIGHLIGHTS OF PRESCRIBING INFORMATION

These highlights do not include all the information needed to use VIMIZIM safely and effectively. See full prescribing information for VIMIZIM.
VIMIZIM (elosulfase alfa) injection, for intravenous use
Initial U.S. Approval: 2014

WARNING: HYPERSENSITIVITY REACTIONS INCLUDING ANAPHYLAXIS and RISK OF ACUTE RESPIRATORY COMPLICATIONS

See full prescribing information for complete boxed warning.

- Anaphylaxis has occurred during the early course of enzyme replacement therapy and after extended duration of therapy. (5.1)
- Initiate VIMIZIM in a healthcare setting with appropriate medical monitoring and support measures, including access to cardiopulmonary resuscitation equipment. (5.1)
- If a severe hypersensitivity reaction (anaphylaxis) occurs, discontinue VIMIZIM and immediately initiate appropriate medical treatment, including use of epinephrine. (5.1)
- Patients with acute respiratory illness may be at risk of serious acute exacerbation of their respiratory compromise due to hypersensitivity reactions, and require additional monitoring (5.2)

RECENT MAJOR CHANGES

Boxed Warning | 10/2025
Dosage and Administration (2) | 10/2025
Warnings and Precautions (5.1) | 10/2025

1 INDICATIONS AND USAGE

VIMIZIM is a hydrolytic lysosomal glycosaminoglycan (GAG)-specific enzyme indicated for patients with Mucopolysaccharidosis type IVA (MPS IVA; Morquio A syndrome). (1)

2 DOSAGE AND ADMINISTRATION

Administration of VIMIZIM should be supervised by a healthcare provider knowledgeable in the management of hypersensitivity reactions including anaphylaxis. (2.1)

2 mg per kg body weight administered once every week as an intravenous infusion over a minimum of 3.5 to 4.5 hours, based on infusion volume. (2.2, 2.4)

See the full prescribing information for administration modifications due to hypersensitivity reactions. (2.3)

3 DOSAGE FORMS AND STRENGTHS

Injection: 5 mg/5 mL (1 mg/mL) in single-dose vials. (3)

4 CONTRAINDICATIONS

None. (4)

5 WARNINGS AND PRECAUTIONS

- Risk of Acute Respiratory Complications: Patients with acute febrile or respiratory illness may be at higher risk of life-threatening complications from hypersensitivity reactions. Careful consideration should be given to the patient's clinical status prior to administration of VIMIZIM and consider delaying the VIMIZIM infusion. (5.2)

6 ADVERSE REACTIONS

Most common adverse reactions (≥10%) are: pyrexia, vomiting, headache, nausea, abdominal pain, chills, and fatigue. (6.1)

To report SUSPECTED ADVERSE REACTIONS, contact BioMarin at 1-866-906-6100 or FDA at 1-800-FDA-1088 or www.fda.gov/medwatch.

FULL PRESCRIBING INFORMATION

WARNING: HYPERSENSITIVITY REACTIONS INCLUDING ANAPHYLAXIS and RISK OF ACUTE RESPIRATORY COMPLICATIONS

Patients treated with enzyme replacement therapies have experienced life-threatening hypersensitivity reactions, including anaphylaxis. Anaphylaxis has occurred during the early course of enzyme replacement therapy and after extended duration of therapy.

Initiate VIMIZIM in a healthcare setting with appropriate medical monitoring and support measures, including access to cardiopulmonary resuscitation equipment. If a severe hypersensitivity reaction (e.g., anaphylaxis) occurs, discontinue VIMIZIM and immediately initiate appropriate medical treatment, including use of epinephrine. Inform patients of the symptoms of life-threatening hypersensitivity reactions, including anaphylaxis and to seek immediate medical care should symptoms occur [see Warnings and Precautions (5.1)].

Patients with acute respiratory illness may be at risk of serious acute exacerbation of their respiratory compromise due to hypersensitivity reactions and require additional monitoring [see Warnings and Precautions (5.2)].

1 INDICATIONS AND USAGE

VIMIZIM (elosulfase alfa) is indicated for patients with Mucopolysaccharidosis type IVA (MPS IVA; Morquio A syndrome).

2 DOSAGE AND ADMINISTRATION

2.1 Important Administration Instructions

- Administration of VIMIZIM should be supervised by a healthcare provider knowledgeable in the management of hypersensitivity reactions including anaphylaxis [see Warnings and Precautions (5.1)].
- Initiate VIMIZIM in a healthcare setting with appropriate medical monitoring and support measures, including access to cardiopulmonary resuscitation [see Warnings and Precautions (5.1)].
- This product must be diluted prior to administration and administered using a low-protein binding infusion set equipped with a low-protein binding 0.2 micrometer (µm) in-line filter.
- Consider pre-medicating with antihistamines, with or without antipyretics, 30 to 60 minutes prior to the start of the infusion [see Warnings and Precautions (5.1)].

2.2 Recommended Dosage

The recommended dosage of VIMIZIM is 2 mg/kg administered intravenously over a minimum range of 3.5 to 4.5 hours (based on infusion volume) once every week.

2.3 Administration Modifications Due to Hypersensitivity Reaction

In the event of a severe hypersensitivity reaction (e.g., anaphylaxis), discontinue the VIMIZIM infusion and immediately initiate appropriate medical treatment, including use of epinephrine. In the event of a mild to moderate hypersensitivity reaction, consider slowing or temporarily interrupting the infusion, or administering additional antihistamines, antipyretics, and/or corticosteroids [see Warnings and Precautions (5.1)].

2.4 Preparation Instructions

Use aseptic technique during preparation.

1. Determine the number of VIMIZIM vials based on the patient's actual body weight in kg and the recommended dose [see Dosage and Administration (2.2)].
2. Remove vials from the refrigerator.
3. Select the appropriate size 0.9% Sodium Chloride Injection, USP infusion bag and calculate the infusion volume based on patient's actual body weight:
  1. For patients who weigh less than 25 kg, the final infusion volume should be 100 mL
  2. For patients who weigh 25 kg or more, the final infusion volume should be 250 mL.
4. Withdraw and discard a volume of 0.9% Sodium Chloride Injection, USP from either the 100 mL or 250 mL infusion bag equal to the volume of VIMIZIM to be added.
5. Withdraw the required volume of VIMIZIM from the vial(s) and add to the 0.9% Sodium Chloride Injection, USP infusion bag. Gently rotate the infusion bag to mix the diluted solution. Avoid vigorous shaking or agitation. Discard unused portion remaining in the vial(s).
6. Visually inspect the solution for particulate matter and discoloration. The solution should be clear to slightly opalescent and colorless to pale yellow. The diluted VIMIZIM solution may contain proteinaceous particles in the form of translucent fibers which will be removed by the in-line filter during infusion. Discard if opaque particles are present or the solution is discolored.

2.5 Administration Instructions

Use an infusion set equipped with a low-protein binding 0.2 micrometer (µm) in-line filter to administer VIMIZIM.

Do not infuse with other products in the infusion tubing. Compatibility with other products has not been evaluated.

Table 1. Intravenous Infusion Rate for VIMIZIM Based on Patient Weight
Patient Weight (kg) | Infusion rate (mL/hour)
Patient Weight (kg) | Initial Rate (first 15 minutes) | Subsequent Rate (next 15 minutes) | Subsequent Rate Increments [If tolerated, the infusion rate can be increased incrementally up to the maximum infusion rate.] | Maximum Infusion Rate
Less than 25 kg | 3 mL/hour | 6 mL/hour | 6 mL/hour every 15 minutes | 36 mL/hour
25 kg or more | 6 mL/hour | 12 mL/hour | 12 mL/hour every 15 minutes | 72 mL/hour

Table 2. Minimum Infusion Time for VIMIZIM Based on Patient Weight
Patient Weight (kg) | Minimum Infusion Time (hours)
Less than 25 kg | 3.5 hours
25 kg or more | 4.5 hours

2.6 Storage of the Diluted Solution

- If the diluted VIMIZIM solution is not used immediately:
  - Store the diluted solution refrigerated at 2°C to 8°C (36°F to 46°F) for up to 24 hours or at room temperature between 23°C to 27°C (73°F to 81°F) for up to 24 hours.
- Diluted VIMIZIM solution must be used within 48 hours, inclusive of total infusion time.
- Discard if not used within 48 hours.
- Do not freeze or shake.

3 DOSAGE FORMS AND STRENGTHS

Injection: 5 mg/5 mL (1 mg/mL) as a clear to slightly opalescent and colorless to pale yellow solution in a single-dose vial.

4 CONTRAINDICATIONS

None.

5 WARNINGS AND PRECAUTIONS

5.1 Hypersensitivity Reactions Including Anaphylaxis

Life-threatening hypersensitivity reactions, including anaphylaxis, have been reported in patients treated with enzyme replacement therapies, including VIMIZIM. In premarketing clinical trials, 18 of 235 (7.7%) patients treated with VIMIZIM experienced signs and symptoms consistent with anaphylaxis. These 18 patients experienced 26 anaphylactic reactions during infusion with signs and symptoms including cough, erythema, throat tightness, urticaria, flushing, cyanosis, hypotension, rash, dyspnea, chest discomfort, and gastrointestinal symptoms (e.g., nausea, abdominal pain, retching, and vomiting) in conjunction with urticaria. These cases of anaphylaxis occurred as early as 30 minutes from the start of infusion and up to three hours after infusion. Anaphylaxis occurred as late into treatment as the 47th infusion.

In clinical trials with VIMIZIM, 44 of 235 (18.7%) patients experienced hypersensitivity reactions, including anaphylaxis. Hypersensitivity reactions have occurred as early as 30 minutes from the start of infusion but as late as six days after infusion. Frequent symptoms of hypersensitivity reactions (occurring in more than 2 patients) included anaphylactic reactions, urticaria, peripheral edema, cough, dyspnea, and flushing.

Anaphylaxis has occurred during the early course of enzyme replacement therapy and after extended duration of therapy. Administration of VIMIZIM should be supervised by a healthcare provider knowledgeable in the management of hypersensitivity reactions including anaphylaxis. Initiate VIMIZIM in a healthcare setting with appropriate medical monitoring and support measures, including access to cardiopulmonary resuscitation equipment. Observe patients closely for an appropriate period of time after administration of VIMIZIM, taking into account the time to onset of anaphylaxis seen in premarketing clinical trials.

Because of the potential for hypersensitivity reactions, administer antihistamines with or without antipyretics prior to infusion. Management of hypersensitivity reactions should be based on the severity of the reaction and include slowing or temporarily interrupting the infusion, and/or administering additional antihistamines, antipyretics, and/or corticosteroids for mild to moderate reactions. If a severe hypersensitivity reaction (e.g., anaphylaxis) occurs, discontinue VIMIZIM and immediately initiate appropriate medical treatment, including use of epinephrine. Inform patients of the symptoms of life-threatening hypersensitivity reactions, including anaphylaxis and to seek immediate medical care should symptoms occur.

Consider the risks and benefits of re-administering VIMIZIM following a severe reaction.

5.2 Risk of Acute Respiratory Complications

Patients with acute febrile or respiratory illness at the time of VIMIZIM infusion may be at higher risk of life-threatening complications from hypersensitivity reactions. Careful consideration should be given to the patient's clinical status prior to administration of VIMIZIM and consider delaying the VIMIZIM infusion.

Sleep apnea is common in MPS IVA patients. Evaluation of airway patency should be considered prior to initiation of treatment with VIMIZIM. Patients using supplemental oxygen or continuous positive airway pressure (CPAP) during sleep should have these treatments readily available during infusion in the event of an acute reaction, or extreme drowsiness/sleep induced by antihistamine use.

5.3 Spinal or Cervical Cord Compression

Spinal or cervical cord compression (SCC) is a known and serious complication of MPS IVA and may occur as part of the natural history of the disease. In clinical trials, SCC was observed both in patients receiving VIMIZIM and patients receiving placebo. Patients with MPS IVA should be monitored for signs and symptoms of SCC (including back pain, paralysis of limbs below the level of compression, urinary and fecal incontinence) and given appropriate clinical care.

6 ADVERSE REACTIONS

The following serious adverse reactions are described below and elsewhere in the labeling:

- Hypersensitivity Reactions Including Anaphylaxis [see Warnings and Precautions (5.1)].
- Risk of Acute Respiratory Complications [see Warnings and Precautions (5.2)].
- Spinal or Cervical Cord Compression [see Warnings and Precautions (5.3)].

6.1 Clinical Trials Experience

Because clinical trials are conducted under widely varying conditions, adverse reaction rates observed in the clinical trials of a drug cannot be directly compared to rates in the clinical trials of another drug and may not reflect the rates observed in practice.

A 24-week, randomized, double-blind, placebo-controlled clinical trial of VIMIZIM was conducted in 176 patients with MPS IVA, ages 5 to 57 years old. Approximately half of the patients (49%) were male. Of the 176 patients, 65% were White, 23% Asian, 3% Black, and 10% Other race. The majority of patients (78%) were non-Hispanic. Patients were randomized to three treatment groups: VIMIZIM 2 mg/kg once per week (n=58), VIMIZIM 2 mg/kg once every other week (n=59), or placebo (n=59). All patients were treated with antihistamines prior to each infusion.

Table 3 summarizes the most common adverse reactions that occurred in the placebo-controlled trial with an incidence of ≥ 10% in patients treated with VIMIZIM 2 mg/kg once per week and with a higher incidence than in the placebo-treated patients.

Table 3: Adverse Reactions That Occurred in the Placebo-Controlled Trial in At Least 10% of Patients in the VIMIZIM 2 mg/kg Once Per Week Group and with a Higher Incidence than in the Placebo Group
Adverse Reaction | VIMIZIM 2 mg/kg once per week | Placebo
 | N= 58 n (%) | N= 59 n (%)
Pyrexia | 19 (33%) | 8 (14%)
Vomiting | 18 (31%) | 4 (7%)
Headache | 15 (26%) | 9 (15%)
Nausea | 14 (24%) | 4 (7%)
Abdominal pain | 12 (21%) | 1 (2%)
Chills | 6 (10%) | 1 (2%)
Fatigue | 6 (10%) | 2 (3%)

Extension Trial

An open-label extension trial was conducted in 173 patients who completed the placebo-controlled trial [see Clinical Studies (14)]. No new adverse reactions were reported.

6.2 Immunogenicity

As with all therapeutic proteins, including VIMIZIM, there is potential for immunogenicity. The detection of antibody formation is highly dependent on the sensitivity and specificity of the assay. Additionally, the observed incidence of antibody (including neutralizing antibody) positivity in an assay may be influenced by several factors including assay methodology, sample handling, timing of sample collection, concomitant medications, and underlying disease. For these reasons, comparison of the incidence of antibodies in other studies or to other elosulfase alfa products may be misleading.

All patients treated with VIMIZIM 2 mg/kg once per week in the placebo-controlled trial developed anti-drug antibodies by Week 4. Anti-drug antibody titers were sustained or increased for the duration of VIMIZIM treatment. Because all patients developed anti-drug antibodies, associations between antibody titers and reductions in treatment effect or the occurrence of anaphylaxis or other hypersensitivity reactions could not be determined.

All patients treated with VIMIZIM 2 mg/kg once per week tested positive for neutralizing antibodies capable of inhibiting the drug from binding to the mannose-6-phosphate receptor at least once during the trial. Binding to this receptor is required for VIMIZIM to be taken into cells where it is active. Neutralizing antibody titers were not determined in the patients. Therefore, the possibility of an association between neutralizing antibody titer and treatment effect cannot be assessed.

8 USE IN SPECIFIC POPULATIONS

8.1 Pregnancy

Risk Summary

Available data from published case reports, a registry with a pregnancy sub-study and pharmacovigilance reports with VIMIZIM use during pregnancy have not identified a drug-associated risk of major birth defects, miscarriage, or adverse maternal or fetal outcomes. Limitations of the available data include a small number of exposed cases and missing data.

In animal reproduction studies, no effects on embryo-fetal development were observed in rats given daily administration of elosulfase alfa up to 33 times the human steady-state AUC (area under the concentration-time curve) at the recommended human weekly dose pre-mating and through the period of organogenesis. No effects on embryo-fetal development were observed in rabbits given daily administration of elosulfase alfa at doses up to 8 times the human steady-state AUC at the recommended weekly dose during organogenesis, which produced maternal toxicity. A dose-dependent increase in stillbirths was observed when elosulfase alfa was administered daily in rats during organogenesis through lactation at doses 5 times the human steady-state AUC at the recommended human weekly dose. An increase in pup mortality was observed at doses producing maternal toxicity.

The background risk of major birth defects and miscarriage for the indicated population is unknown. All pregnancies have a background risk of birth defect, loss, or other adverse outcomes. In the U.S. general population, the estimated background risk of major birth defects and miscarriage in clinically recognized pregnancies is 2 to 4% and 15 to 20%, respectively.

Clinical Considerations

Disease-associated maternal and embryo/fetal risk

Pregnancy can exacerbate preexisting clinical manifestations of MPS and lead to adverse outcomes for both mother and fetus.

Data

Animal Data

All reproductive studies with rats included pre-treatment with diphenhydramine to prevent or minimize hypersensitivity reactions. The effects of elosulfase alfa were evaluated based on comparison to a control group treated with diphenhydramine alone. Daily intravenous administration of up to 20 mg/kg elosulfase alfa in rats (33 times the human steady-state AUC at the recommended weekly dose of 2 mg/kg) during a 15-day pre-mating period, mating, and the period of organogenesis, produced no maternal toxicity or effects on embryo-fetal development. Daily intravenous administration of up to 10 mg/kg in rabbits (8 times the human steady-state AUC at the recommended weekly dose) during the period of organogenesis had no effects on embryo-fetal development. However, maternal toxicity (gross changes in liver) was observed in rabbits given doses of 1 mg/kg/day and higher (0.1 times the human steady-state AUC at the recommended weekly dose). Elosulfase alfa produced an increase in the percentage of stillbirths when administered daily to rats at intravenous doses of 6 mg/kg and higher (5 times the human steady-state AUC at the recommended weekly dose) during the period of organogenesis through lactation. Daily intravenous administration of 20 mg/kg (33 times the human steady-state AUC at the recommended weekly dose) produced maternal toxicity and an increase in mortality of offspring during the lactation period. This study lacked a full evaluation of neurodevelopmental milestones; however, no effects of elosulfase alfa were noted in tests for learning and memory.

8.2 Lactation

Risk Summary

There are no data on the presence of elosulfase alfa in human milk, the effects on the breastfed infant, or the effects on milk production. Elosulfase alfa is present in milk from treated rats (see Data). When a drug is present in animal milk, it is likely that the drug will be present in human milk. The developmental and health benefits of breastfeeding should be considered along with the mother's clinical need for VIMIZIM and any potential adverse effects on the breastfed infant from VIMIZIM or from the underlying maternal condition.

Data

Elosulfase alfa was detected in 1 of 5 milk samples from rat dams administered 6 mg/kg/day elosulfase alfa and 4 of 5 milk samples from dams administered 20 mg/kg/day elosulfase alfa. The concentration of drug in animal milk does not necessarily predict the concentration of drug in human milk.

8.4 Pediatric Use

Safety and effectiveness of VIMIZIM have been established in pediatric patients 5 years of age and older. Use of VIMIZIM in patients 5 years of age and older is supported by an adequate and well-controlled trial in pediatric and adult patients. Clinical trials with VIMIZIM were conducted in 176 patients (median age 12 years, range 5 to 57 years old) with the majority of patients in the pediatric age group (53% aged 5 to 11 years, 27% aged 12 to 17 years) [see Clinical Studies (14)]. Safety and effectiveness in pediatric patients below 5 years of age have not been established.

8.5 Geriatric Use

Clinical studies of VIMIZIM did not include any patients aged 65 and over. It is not known whether they respond differently from younger patients.

11 DESCRIPTION

Elosulfase alfa is a purified human enzyme produced by recombinant DNA technology in a Chinese hamster ovary cell line. Human N-acetylgalactosamine-6-sulfatase (EC 3.1.6.4) is a hydrolytic lysosomal glycosaminoglycan-specific enzyme that hydrolyzes sulfate from either galactose-6-sulfate or N-acetyl-galactosamine-6-sulfate on the non-reducing ends of the glycosaminoglycans keratan sulfate (KS) and chondroitin-6-sulfate (C6S).

Elosulfase alfa is a soluble glycosylated dimeric protein with two oligosaccharide chains per monomer. Each monomeric peptide chain contains 496 amino acids and has an approximate molecular mass of 55 kDa (59 kDa including the oligosaccharides). One of the oligosaccharide chains contains bis-mannose-6-phosphate (bisM6P). bisM6P binds a receptor at the cell surface and the binding mediates cellular uptake of the protein to the lysosome. Elosulfase alfa has a specific activity of 2.6 to 6.0 units/mg. One activity unit is defined as the amount of the enzyme required to convert 1 micromole of sulfated monosaccharide substrate D-galactopyranoside-6-sulfate (Gal-6S) to de-sulfated-galactose (Gal) and free sulfate per minute at 37°C.

VIMIZIM (elosulfase alfa) injection is a sterile, preservative-free, nonpyrogenic, clear to slightly opalescent, colorless to pale yellow solution for intravenous infusion after dilution. Each single-dose vial contains 5 mL solution of 5 mg elosulfase alfa, 31.6 mg arginine hydrochloride, 34.5 mg monobasic sodium phosphate, 0.5 mg polysorbate 20, 8.2 mg sodium acetate, and 100 mg sorbitol in Water for Injection, USP with a pH between 5 to 5.8.

12 CLINICAL PHARMACOLOGY

12.1 Mechanism of Action

Mucopolysaccharidoses comprise a group of lysosomal storage disorders caused by the deficiency of specific lysosomal enzymes required for the catabolism of glycosaminoglycans (GAG). Mucopolysaccharidosis IVA (MPS IVA, Morquio A Syndrome) is characterized by the absence or marked reduction in N-acetylgalactosamine-6-sulfatase activity. The sulfatase activity deficiency results in the accumulation of the GAG substrates, KS and C6S, in the lysosomal compartment of cells throughout the body. The accumulation leads to widespread cellular, tissue, and organ dysfunction. VIMIZIM is intended to provide the exogenous enzyme N-acetylgalactosamine-6-sulfatase that will be taken up into the lysosomes and increase the catabolism of the GAGs KS and C6S. Elosulfase alfa uptake by cells into lysosomes is mediated by the binding of mannose-6-phosphate-terminated oligosaccharide chains of elosulfase alfa to mannose-6-phosphate receptors.

In the absence of an animal disease model that recapitulates the human disease phenotype, elosulfase alfa pharmacological activity was evaluated using human primary chondrocytes from two MPS IVA patients. Treatment of MPS IVA chondrocytes with elosulfase alfa induced clearance of KS lysosomal storage from the chondrocytes.

12.2 Pharmacodynamics

The pharmacodynamic effect of VIMIZIM was assessed by reductions in urinary KS levels. The relationship of urinary KS to other measures of clinical response has not been established [see Clinical Studies (14)]. No association was observed between antibody development and urinary KS levels.

12.3 Pharmacokinetics

The pharmacokinetics of elosulfase alfa were evaluated in 23 patients with MPS IVA who received intravenous infusions of VIMIZIM 2 mg/kg once weekly, over approximately 4 hours, for 22 weeks. Eleven patients were aged 5 to 11 years, six were aged 12 to 17 years, and six were aged 18 to 41 years. Table 4 summarizes the pharmacokinetic parameters at Week 0 and Week 22. Mean AUC0-t and Cmax increased to 2.8- and 2.9-fold, respectively, at Week 22 compared to Week 0. Mean t1/2 increased from 7.5 min at Week 0 to 35.9 min at Week 22. These changes are likely related to the development of neutralizing antibodies in all patients.

Table 4: Pharmacokinetic Parameters
Pharmacokinetic Parameter | Week 0 (N = 22) [The pharmacokinetics of elosulfase alfa was evaluated in 23 individual patients. However, 1 patient was not tested at Week 0 and another patient was not tested at Week 22;] Mean (SD) | Week 22 (N = 22) Mean (SD)
AUC0-t, min × mcg/mL [AUC0-t, area under the plasma concentration-time curve from time zero to the time of last measurable concentration;] | 238 (100) | 577 (416)
Cmax, mcg/mL [Cmax, observed maximum plasma concentration;] | 1.49 (0.534) | 4.04 (3.24)
Tmax, min [Tmax, time from zero to maximum plasma concentration;] | 172 (75.3) | 202 (90.8)
CL, mL/min/kg [CL, total clearance of drug after intravenous administration;] | 10.0 (3.73) [N = 15;] | 7.08 (13.0) [N = 20;]
Vdss, mL/kg [Vdss, apparent volume of distribution at steady-state;] | 396 (316) [N = 14;] | 650 (1842)
t1/2, min [t1/2, elimination half-life] | 7.52 (5.48) | 35.9 (21.5)

13 NONCLINICAL TOXICOLOGY

13.1 Carcinogenesis, Mutagenesis, Impairment of Fertility

Long-term studies in animals to evaluate carcinogenic potential or studies to evaluate mutagenic potential have not been performed with elosulfase alfa. Based on the mechanism of action, elosulfase alfa is not expected to be tumorigenic. Daily intravenous administration of elosulfase alfa in rats at doses up to 20 mg/kg (55 times the human steady-state AUC in male rats and 33 times the human steady-state AUC in female rats at the recommended human weekly dose) had no effects on fertility or reproductive performance.

14 CLINICAL STUDIES

The safety and efficacy of VIMIZIM were assessed in a 24-week, randomized, double-blind, placebo-controlled clinical trial of 176 patients with MPS IVA. The age of patients ranged from 5 to 57 years. The majority of the patients (82%) presented with a medical history of musculoskeletal conditions, which includes knee deformity (52%), kyphosis (31%), hip dysplasia (22%), prior spinal fusion surgery (22%) and arthralgia (20%). At baseline, all enrolled patients could walk more than 30 meters (m) but less than 325 m in six minutes.

Patients received VIMIZIM 2 mg/kg once per week (n=58), VIMIZIM 2 mg/kg once every other week (n=59), or placebo (n=59).

The primary endpoint was the change from baseline in the distance walked in six minutes (six-minute walk test, 6-MWT) at Week 24. The other endpoints included changes from baseline in the rate of stair climbing in three minutes (three-minute stair climb test, 3-MSCT) and changes from baseline in urine KS levels at Week 24. The treatment effect in the distance walked in 6 minutes, compared to placebo, was 22.5 m (CI95, 4.0, 40.9; p=0.0174) in patients who received VIMIZIM 2 mg/kg once per week. There was no difference in the rate of stair climbing between patients who received VIMIZIM 2 mg/kg once per week and those who received placebo. Patients who received VIMIZIM 2 mg/kg once every other week performed similarly in the 6-MWT and 3-MSCT as those who received placebo. The reduction in urinary KS levels from baseline, a measure of pharmacodynamic effect, was greater in the VIMIZIM treatment groups compared to placebo. The relationship between urinary KS and other measures of clinical response has not been established.

Table 5: Results from Placebo-Controlled Clinical Trial
 | VIMIZIM 2 mg/kg once per week |  |  | Placebo |  |  | VIMIZIM vs. Placebo
 | Baseline | Week 24 | Change | Baseline | Week 24 | Change | Mean Difference in Changes
N | 58 | 57 [One patient in the VIMIZIM group dropped out after 1 infusion] | 57 | 59 | 59 | 59
Six-Minute Walk Test (Meters)
Mean ± SD | 203.9 ± 76.32 | 243.3 ± 83.53 | 36.5 ± 58.49 | 211.9 ± 69.88 | 225.4 ± 83.22 | 13.5 ± 50.63 | 23.0 [Observed VIMIZIM mean change – Placebo mean change] (CI95, 2.9, 43.1)
Median | 216.5 | 251.0 | 20.0 | 228.9 | 229.4 | 9.9 | 22.5 [ANCOVA Model-based VIMIZIM mean change – Placebo mean change, adjusted for baseline 6MWT categories (less than or equal to 200 meters, greater than 200 meters) and age groups (5-11, 12-18, 19 or older)] (CI95, 4.0, 40.9)
Min, Max | 42.4, 321.5 | 52.0, 399.9 | -57.8, 228.7 | 36.2, 312.2 | 50.6, 501.0 | -99.2, 220.5 | (p = 0.0174), [p-value based on the model-based difference in means]

Extension Trial

Patients who participated in the placebo-controlled trial were eligible to continue treatment in an open-label extension trial. One hundred seventy-three of 176 patients enrolled in the extension trial in which patients received VIMIZIM 2 mg/kg once per week (n=86) or VIMIZIM 2 mg/kg once every other week (n=87). In patients who continued to receive VIMIZIM 2 mg/kg once per week for another 48 weeks (for a total of 72-week exposure), walking ability showed no further improvement beyond the first 24 weeks of treatment in the placebo-controlled trial.

16 HOW SUPPLIED/STORAGE AND HANDLING

How Supplied

VIMIZIM (elosulfase alfa) injection is supplied as a sterile, preservative-free, clear to slightly opalescent, clear to pale yellow solution in a single-dose vial. Each vial contains 5 mg/5 mL (1 mg/mL) of elosulfase alfa. VIMIZIM is available as:

One single-dose vial in a carton (NDC 68135-100-01)

Storage and Handling

Store refrigerated at 2°C to 8°C (36°F to 46°F) in the original carton to protect from light. Do not freeze or shake.

17 PATIENT COUNSELING INFORMATION

Hypersensitivity Reactions Including Anaphylaxis

Advise the patient or caregiver that life-threatening hypersensitivity reactions, including anaphylaxis may occur with VIMIZIM treatment.

Advise the patient or caregiver that anaphylaxis has occurred during the early course of enzyme replacement therapy and after 1extended duration of therapy.

Inform the patient or caregiver of the symptoms of life-threatening hypersensitivity reactions, including anaphylaxis, and to seek immediate medical care should symptoms occur. The risks and benefits of re-administering VIMIZIM following a severe reaction should be considered [see Warnings and Precautions (5.1)].

Manufactured by:
BioMarin Pharmaceutical Inc.
Novato, CA 94949
US License Number 1649
1-866-906-6100 (phone)

PRINCIPAL DISPLAY PANEL - 5 mL Vial Carton

NDC 68135-100-01

Vimizim®
(elosulfase alfa)

Injection

5 mg/5 mL (1 mg/mL)

For Intravenous Infusion
After Dilution

One 5 mL Single-dose vial
Discard unused portion.

Rx Only

BiOMARIN®